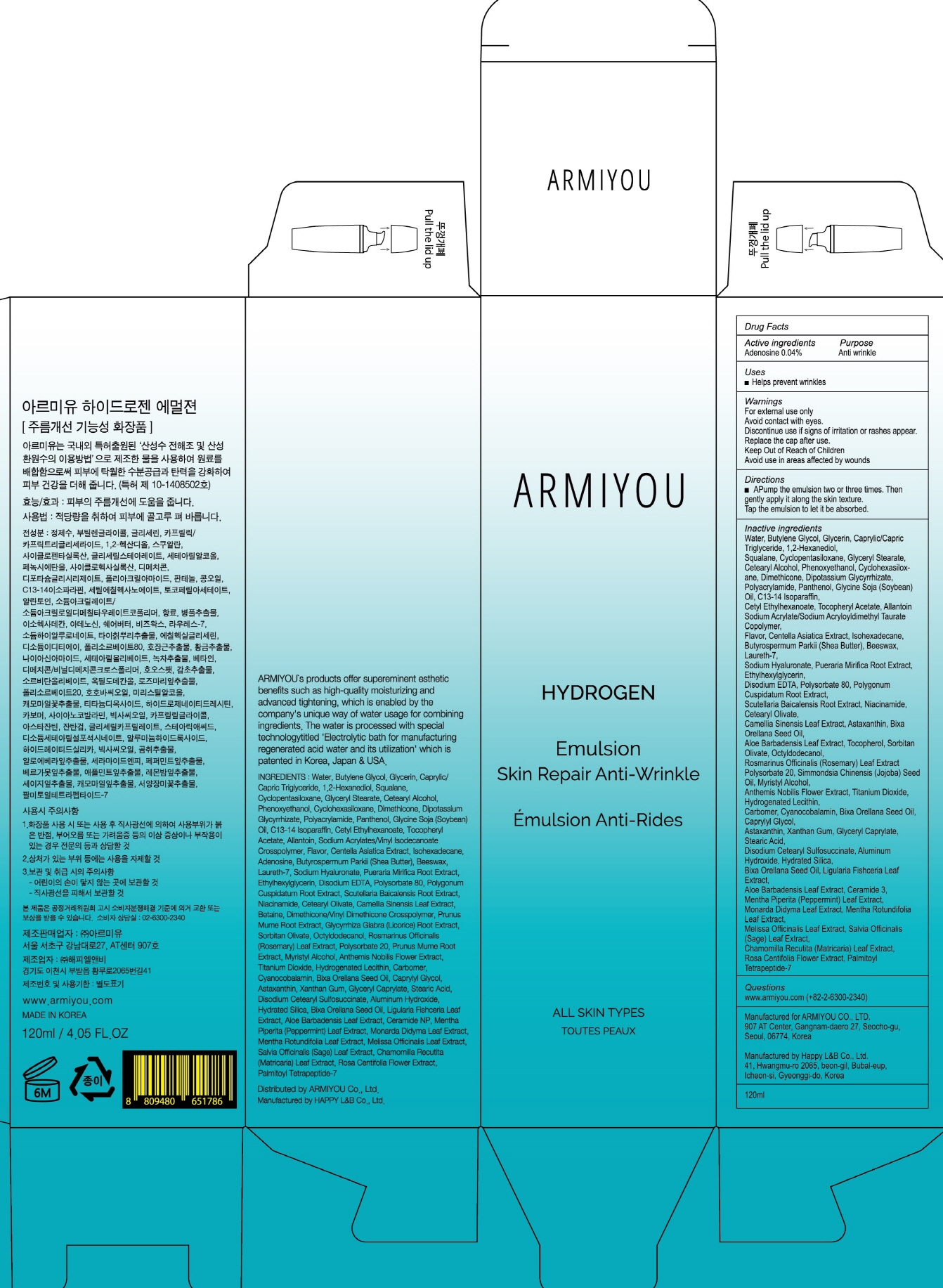 DRUG LABEL: ARMIYOU HYDROGEN
NDC: 71878-030 | Form: EMULSION
Manufacturer: Armiyou
Category: otc | Type: HUMAN OTC DRUG LABEL
Date: 20171122

ACTIVE INGREDIENTS: Adenosine 0.04 g/120 mL
INACTIVE INGREDIENTS: Water; Butylene Glycol

ACTIVE INGREDIENT

Active ingredients: Adenosine 0.04%

INACTIVE INGREDIENT

Inactive ingredients: Water, Butylene Glycol, Glycerin, Caprylic/Capric Triglyceride, 1,2-Hexanediol, Squalane, Cyclopentasiloxane, Glyceryl Stearate, Cetearyl Alcohol, Phenoxyethanol, Cyclohexasiloxane, Dimethicone, Dipotassium Glycyrrhizate, Polyacrylamide, Panthenol, Glycine Soja (Soybean) Oil, C13-14 Isoparaffin, Cetyl Ethylhexanoate, Tocopheryl Acetate, Allantoin Sodium Acrylate/Sodium Acryloyldimethyl Taurate Copolymer, Flavor, Centella Asiatica Extract, Isohexadecane, Butyrospermum Parkii (Shea Butter), Beeswax, Laureth-7, Sodium Hyaluronate, Pueraria Mirifica Root Extract, Ethylhexylglycerin, Disodium EDTA, Polysorbate 80, Polygonum Cuspidatum Root Extract, Scutellaria Baicalensis Root Extract, Niacinamide, Cetearyl Olivate, Camellia Sinensis Leaf Extract, Astaxanthin, Bixa Orellana Seed Oil, Aloe Barbadensis Leaf Extract, Tocopherol, Sorbitan Olivate, Octyldodecanol, Rosmarinus Officinalis (Rosemary) Leaf Extract Polysorbate 20, Simmondsia Chinensis (Jojoba) Seed Oil, Myristyl Alcohol, Anthemis Nobilis Flower Extract, Titanium Dioxide, Hydrogenated Lecithin, Carbomer, Cyanocobalamin, Bixa Orellana Seed Oil, Caprylyl Glycol, Astaxanthin, Xanthan Gum, Glyceryl Caprylate, Stearic Acid, Disodium Cetearyl Sulfosuccinate, Aluminum Hydroxide, Hydrated Silica, Bixa Orellana Seed Oil, Ligularia Fishceria Leaf Extract, Aloe Barbadensis Leaf Extract, Ceramide 3, Mentha Piperita (Peppermint) Leaf Extract, Monarda Didyma Leaf Extract, Mentha Rotundifolia Leaf Extract, Melissa Officinalis Leaf Extract, Salvia Officinalis (Sage) Leaf Extract, Chamomilla Recutita (Matricaria) Leaf Extract, Rosa Centifolia Flower Extract, Palmitoyl Tetrapeptide-7

PURPOSE

Purpose: Anti wrinkle

WARNINGS

Warnings: For external use only Avoid contact with eyes. Discontinue use if signs of irritation or rashes appear. Replace the cap after use. Keep Out of Reach of Children. Avoid use in areas affected by wounds.

KEEP OUT OF REACH OF CHILDREN

Uses

Uses: Helps prevent wrinkles

Directions

Directions: Pump the emulsion two or three times. Then gently apply it along the skin texture. Tap the emulsion to let it be absorbed.